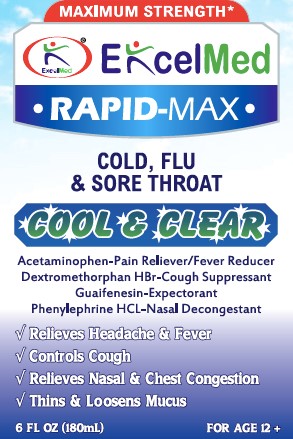 DRUG LABEL: Rapid Max Maximum Strength Cool and Clear - Cold, Flu and Sore throat
NDC: 71027-019 | Form: LIQUID
Manufacturer: KINGSTON PHARMA LLC
Category: otc | Type: HUMAN OTC DRUG LABEL
Date: 20170301

ACTIVE INGREDIENTS: ACETAMINOPHEN 650 mg/20 mL; DEXTROMETHORPHAN HYDROBROMIDE 20 mg/20 mL; GUAIFENESIN 400 mg/20 mL; PHENYLEPHRINE HYDROCHLORIDE 10 mg/20 mL
INACTIVE INGREDIENTS: ANHYDROUS CITRIC ACID; FD&C BLUE NO. 1; FD&C RED NO. 40; SUCRALOSE; GLYCERIN; PROPYLENE GLYCOL; WATER; SODIUM CITRATE, UNSPECIFIED FORM; SODIUM BENZOATE; DISODIUM EDTA-COPPER; XANTHAN GUM; PROPYL GALLATE; SORBITOL

ExcelMed Rapid Max Maximum Strength Cool & Clear- Cold, Flu & Sore throat

Active Ingredient: Each 20ml contains:
Acetaminophen 650 mg
Dextromethorphan 20 mg
Guaifenesin 400 mg
Phenylephrine 10 mg

Purpose:
Pain reliever, Fever Reducer
Cough Suppressant
Expectorant
Nasal Decongestant

Uses

- Temporarily relieves these common cold/flu symptoms
  1. Minor aches and pains
  2. Headache
  3. Sore throat
  4. Nasal congestion
  5. Fever
  6. helps loosen phlegm (mucus) and thin bronchial secretions to rid the bronchial passageways of bothersome mucus and make coughs more productive

DO NOT USE IF PRINTED SAFETY SEAL ON THE BOTTLE IS BROKEN OR MISSING.

Warnings:
Liver warning: This product contains acetaminophen. Severe liver damage may occur if adult/child takes

- More than 4 doses in 24 hours, which is the maximum daily amount for this product.
- With other drugs containing acetaminophen.
- Adult has 3 or more alcoholic drinks every day while using this product.

Sore throat warning: If sore throat is severe, persists for more than 2 days, is accompanied or followed by fever, headache, rash, nausea, or vomiting, consult a doctor promptly.

Do not use

- for children under 12 years of age
- if you are now taking a prescription monoamine oxidase inhibitor (MAOI) (certain drugs for depression, psychiatric or emotional conditions, or Parkinson's disease), or for 2 weeks after stopping the MAOI drug. If you do not know if your prescription drug contains an MAOI, ask a doctor or pharmacist before taking this product.
- with any other drug containing acetaminophen (prescription or nonprescription). If you are not sure whether a drug contains acetaminophen, ask a doctor or pharmacist.
- if you are allergic to acetaminophen or any of the inactive ingredients in this product.

Ask a doctor before use if you have

- diabetes
- liver disease
- heart disease
- thyroid disease
- high blood pressure
- persistent or chronic cough such as occurs with smoking, asthma, chronic bronchitis or emphysema
- cough that occurs with too much phlegm (mucus)
- trouble urinating due to an enlarged prostate gland

Ask a doctor or pharmacist before use if you are

- Taking the blood thinning drug warfarin

When using this product

- Do not exceed recommended dosage (see overdose warning)

Stop use and ask doctor if

- Nervousness, dizziness or sleeplessness occur
- Symptoms get worse or last more than 5 days (children) or 7 days (adults)
- Fever gets worse or lasts more than 3 days
- Redness or swelling is present
- New symptoms occur
- Cough comes back or occurs with rash or headache that lasts

These could be signs of a serious condition

KEEP OUT OF REACH OF CHILDREN

Keep this and all drugs out of the reach of children.

Overdose Warning: In case of accidental overdose, seek professional assistance or contact a Poison control center right away. Quick medical attention is critical for adults as well as children even if you do not notice any signs or symptoms.

If pregnant or breast-feeding, ask a health professional before use.

If pregnant or breast-feeding,
ask a health professional before use.

Directions:

- Do not take more than directed. (see overdose warning)
- Use enclosed dosing cup.
- Do not take more than 4 doses in 24-hours.
- Adults and children 12 years and over: take 2 tablespoons (TBSP) or 30 mL every 4 hours.
- Children 6 to under 12 years: take 1 tablespoon (TBSP) or 15 mL every 4 hours.
- Children 4 to under 6 years: ask a doctor
- Children under 4 years: do not use
- When using other Daytime or Nite time products, carefully read each label to insure correct dosing

Other information

- Store between 20-25 degree Celsius (68-77 degree Fahrenheit)
- Each tablespoon contains: Sodium 50mg

INACTIVE INGREDIENT

Inactive ingredients Anhydrous Citric Acid, Disodium EDTA-Copper, Sodium Benzoate, Sucralose, Sodium Citrate, Propyl Gallate, Xanthan gum, Glycerin, Propylene glycol, Sorbitol, FD&C Blue#1, FD&C Red# 40 and Purified Water.

HOW SUPPLIED

(packs: 6oz) Kingston NDC# 71027-019-06

Manufactured by: Kingston Pharma LLC
5 County Route 42
Massena, NY 13662